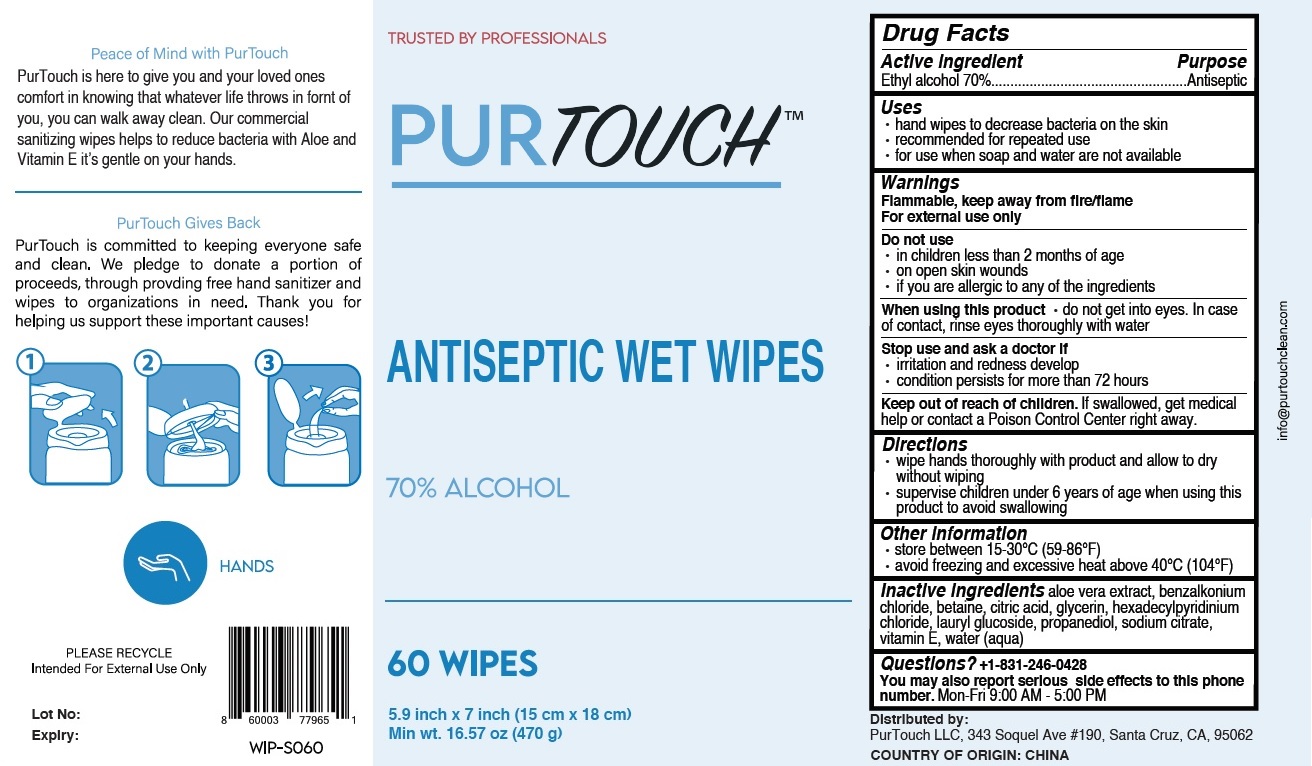 DRUG LABEL: PurTouch Antiseptic Wet Wipes
NDC: 79581-601 | Form: CLOTH
Manufacturer: Purtouch Llc
Category: otc | Type: HUMAN OTC DRUG LABEL
Date: 20200731

ACTIVE INGREDIENTS: ALCOHOL 70 mL/100 mL
INACTIVE INGREDIENTS: ALOE VERA LEAF; BENZALKONIUM CHLORIDE; BETAINE; CITRIC ACID MONOHYDRATE; GLYCERIN; CETYLPYRIDINIUM CHLORIDE ANHYDROUS; LAURYL GLUCOSIDE; PROPANEDIOL; SODIUM CITRATE, UNSPECIFIED FORM; .ALPHA.-TOCOPHEROL; WATER

PURTOUCH ANTISEPTIC WET WIPES

Active ingredient

Ethyl alcohol 70%

Purpose

Antiseptic

Uses

• hand wipes to decrease bacteria on the skin
• recommended for repeated use
• for use when soap and water are not available

Warnings

Flammable, keep away from fire/flame

For external use only

Do not use

• in children less than 2 months of age

• on open skin wounds

• if you are allergic to any of the ingredients

When using this product • do not get into eyes. In case of contact, rinse eyes thoroughly with water

Stop use and ask a doctor if

• irritation and redness develop

• condition persists for more than 72 hours

Keep out of reach of children. If swallowed, get medical help or contact a Poison Control Center right away.

Directions

• wipe hands thoroughly with product and allow to dry without wiping
• supervise children under 6 years of age when using this product to avoid swallowing

Other information

• store between 15-30°C (59-86°F)
• avoid freezing and excessive heat above 40°C (104°F)

INACTIVE INGREDIENT

Inactive ingredients aloe vera extract, benzalkonium chloride, betaine, citric acid, glycerin, hexadecylpyridinium chloride, lauryl glucoside, propanediol, sodium citrate, vitamin E, water (aqua)

Questions? +1-831-246-0428
You may also report serious side effects to this phone number.

Mon-Fri 9:00 AM - 5:00 PM

TRUSTED BY PROFESSIONALS

70% ALCOHOL

Peace of Mind with PurTouch

PurTouch is here to give you and your loved ones comfort in knowing that whatever life throws in front of you, you can walk away clean. Our commercial sanitizing wipes helps to reduce bacteria with Aloe and Vitamin E it’s gentle on your hands.

PurTouch Gives Back

PurTouch is committed to keeping everyone safe and clean. We pledge to donate a portion of proceeds, through providing free hand sanitizer and wipes to organizations in need. Thank you for helping us support these important causes!

HANDS

PLEASE RECYCLE

Intended For External Use Only

Lot No:

Expiry:

Distributed by:
PurTouch LLC, 343 Soquel Ave #190, Santa Cruz, CA, 95062

COUNTRY OF ORIGIN: CHINA

info@purtouchclean.com